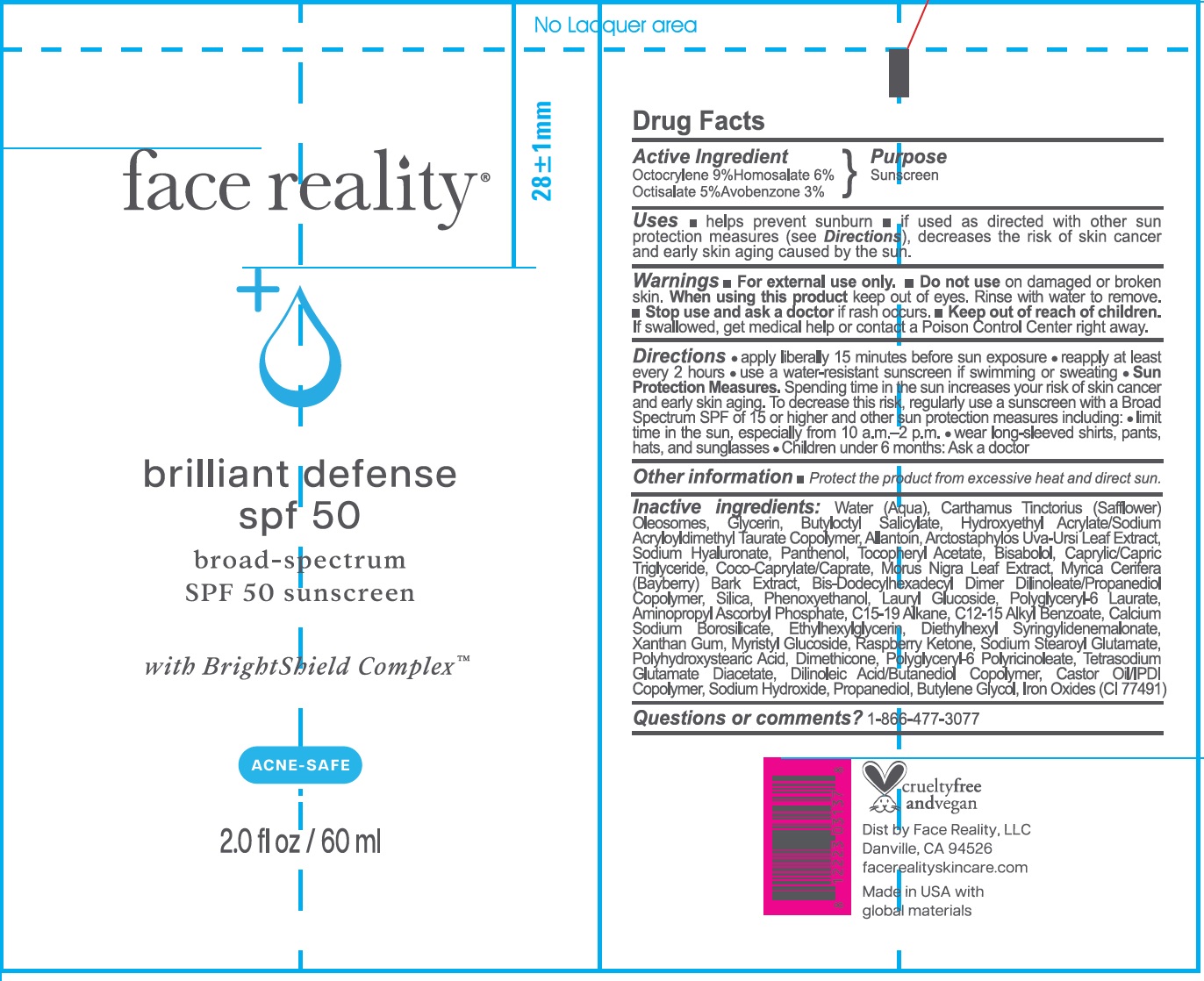 DRUG LABEL: Face Reality Brilliant Defense Sunscreen SPF 50
NDC: 70707-455 | Form: CREAM
Manufacturer: Face Reality, LLC
Category: otc | Type: HUMAN OTC DRUG LABEL
Date: 20250729

ACTIVE INGREDIENTS: OCTOCRYLENE 90 mg/1 mL; HOMOSALATE 60 mg/1 mL; OCTISALATE 50 mg/1 mL; AVOBENZONE 30 mg/1 mL
INACTIVE INGREDIENTS: HYDROXYETHYL ACRYLATE/SODIUM ACRYLOYLDIMETHYL TAURATE COPOLYMER (45000 MPA.S AT 1%); POLYHYDROXYSTEARIC ACID (2300 MW); BIS-DODECYLHEXADECYL DIMER DILINOLEATE/PROPANEDIOL COPOLYMER; C15-19 ALKANE; BUTYLOCTYL SALICYLATE; WATER; CARTHAMUS TINCTORIUS SEED OLEOSOMES; GLYCERIN; ALLANTOIN; ARCTOSTAPHYLOS UVA-URSI LEAF; SODIUM HYALURONATE; PANTHENOL; .ALPHA.-TOCOPHEROL ACETATE; BISABOLOL; MEDIUM-CHAIN TRIGLYCERIDES; COCOYL CAPRYLOCAPRATE; MORUS NIGRA LEAF; MYRICA CERIFERA ROOT BARK; SILICON DIOXIDE; PHENOXYETHANOL; C12-15 ALKYL BENZOATE; LAURYL GLUCOSIDE; POLYGLYCERYL-6 LAURATE; AMINOPROPYL ASCORBYL PHOSPHATE; CALCIUM SODIUM BOROSILICATE; ETHYLHEXYLGLYCERIN; DIETHYLHEXYL SYRINGYLIDENEMALONATE; XANTHAN GUM; MYRISTYL GLUCOSIDE; RASPBERRY KETONE; SODIUM STEAROYL GLUTAMATE; DIMETHICONE; POLYGLYCERYL-6 POLYRICINOLEATE; TETRASODIUM GLUTAMATE DIACETATE; DILINOLEIC ACID/BUTANEDIOL COPOLYMER; CASTOR OIL/IPDI COPOLYMER; SODIUM HYDROXIDE; PROPANEDIOL; BUTYLENE GLYCOL; FERRIC OXIDE RED; BETA-SITOSTEROL

Face Reality Brilliant Defense Sunscreen SPF 50

Active Ingredient

Octocrylene 9% Homosalate 6%
Octisalate 5% Avobenzone 3%

Purpose

Sunscreen

Uses

- helps prevent sunburn
- if used as directed with other sun protection measures (see Directions), decreases the risk of skin cancer and early skin aging caused by the sun.

Warnings

For external use only.

Do not use

- on damaged or broken skin.

When using this product

keep out of eyes. Rinse with water to remove.

Stop use and ask a doctor

- if rash occurs.

Keep out of reach of children.

- If swallowed, get medical help or contact a Poison Control Center right away.

Directions

- apply liberally 15 minutes before sun exposure
- reapply at least every 2 hours
- use a water-resistant sunscreen if swimming or sweating
- Sun Protection Measures.Spending time in the sun increases your risk of skin cancer and early skin aging. To decrease this risk, regularly use a sunscreen with a Broad Spectrum SPF of 15 or higher and other sun protection measures including:
- limit time in the sun, especially from 10 a.m.-2 p.m.
- wear long-sleeved shirts, pants, hats, and sunglasses
- Children under 6 months: Ask a doctor

Other information

- Protect the product from excessive heat and direct sun.

Inactive ingredients:

Water (Aqua), Carthamus Tinctorius (Safflower) Oleosomes, Glycerin, Butyloctyl Salicylate, Hydroxyethyl Acrylate/Sodium Acryloyldimethyl Taurate Copolymer, Allantoin, Arctostaphylos Uva-Ursi Leaf Extract, Sodium Hyaluronate, Panthenol, Tocopheryl Acetate, Bisabolol, Caprylic/Capric Triglyceride, Coco-Caprylate/Caprate, Morus Nigra Leaf Extract, Myrica Cerifera (Bayberry) Bark Extract, Bis-Dodecylhexadecyl Dimer Dilinoleate/Propanediol Copolymer, Silica, Phenoxyethanol, Lauryl Glucoside, Polyglyceryl-6 Laurate, Aminopropyl Ascorbyl Phosphate, C12-15 Alkyl Benzoate, Calcium Sodium Borosilicate, Ethylhexylglycerin, Diethylhexyl Syringylidenemalonate, Xanthan Gum, Myristyl Glucoside, Raspberry Ketone, Sodium Stearoyl Glutamate, Polyhydroxystearic Acid, Dimethicone, Polyglyceryl-6 Polyricinoleate, Tetrasodium Glutamate Diacetate, Dilinoleic Acid/Butanediol Copolymer, Castor Oil/IPDI Copolymer, Sodium Hydroxide, Propanediol, Butylene Glycol, Iron Oxide (CI 77491)

Questions or comments?

1-866-477-3077